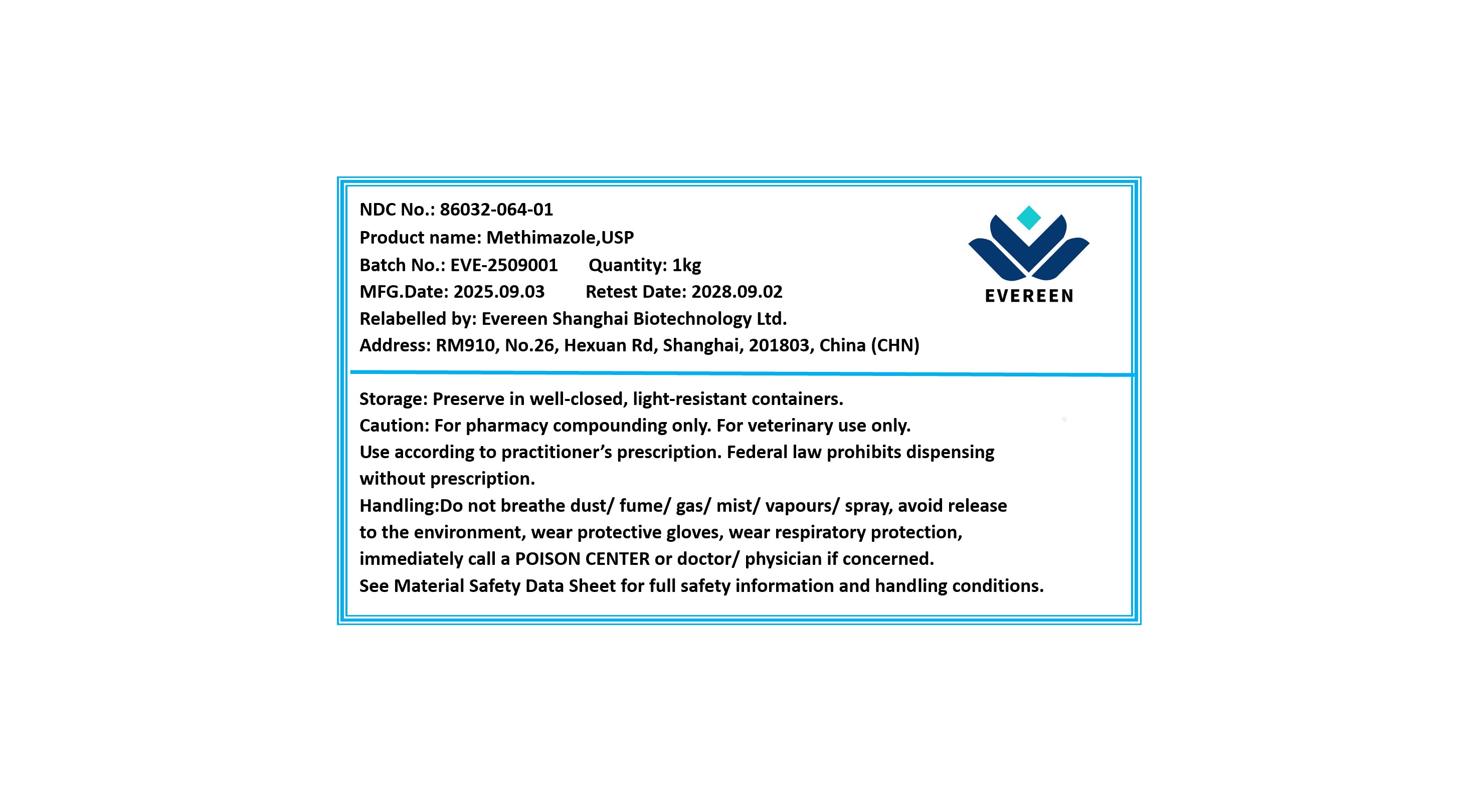 DRUG LABEL: Methimazole
NDC: 86032-064 | Form: POWDER
Manufacturer: Evereen Shanghai Biotechnology Ltd.
Category: other | Type: BULK INGREDIENT - ANIMAL DRUG
Date: 20251114

ACTIVE INGREDIENTS: METHIMAZOLE 1 kg/1 kg

Methimazole